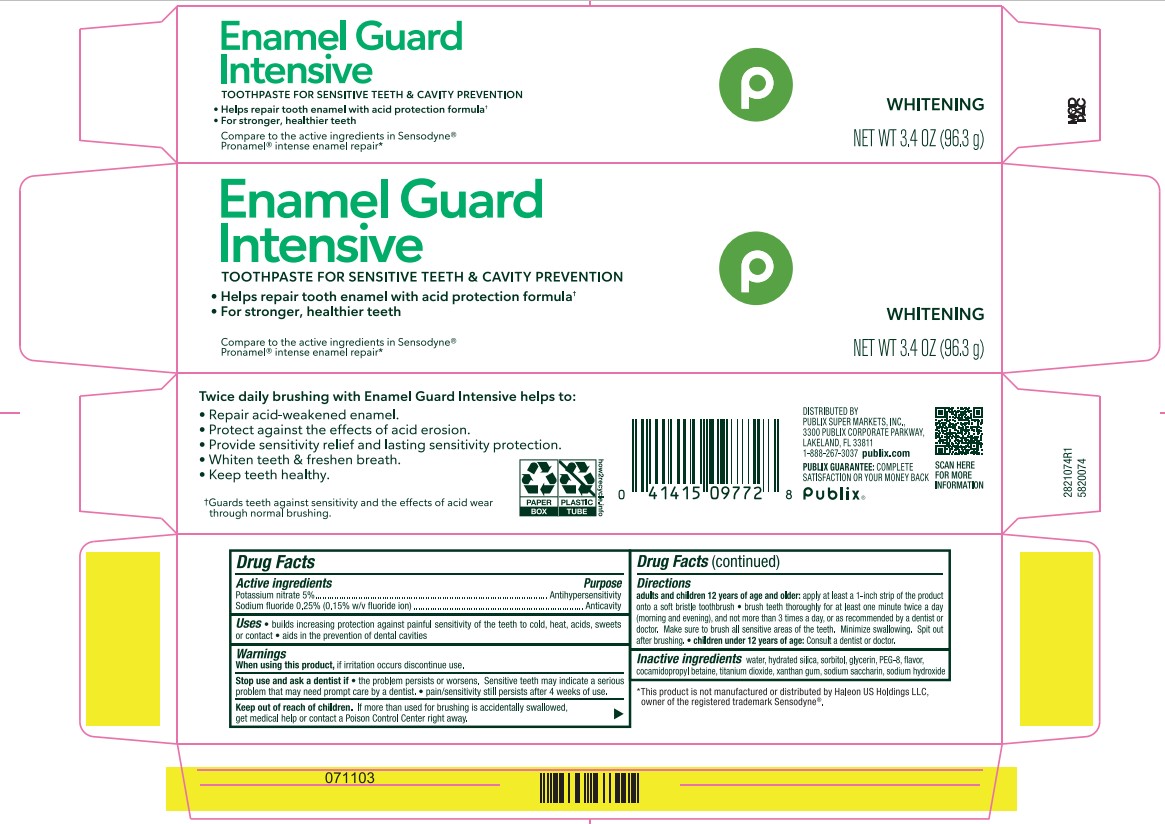 DRUG LABEL: Pronamel Repair Whitening
NDC: 56062-514 | Form: PASTE, DENTIFRICE
Manufacturer: Publix Super Market Inc
Category: otc | Type: HUMAN OTC DRUG LABEL
Date: 20251113

ACTIVE INGREDIENTS: POTASSIUM NITRATE 5 g/100 g; SODIUM FLUORIDE 0.15 g/100 g
INACTIVE INGREDIENTS: WATER; SACCHARIN SODIUM; TITANIUM DIOXIDE; XANTHAN GUM; HYDRATED SILICA; SODIUM HYDROXIDE; COCAMIDOPROPYL BETAINE; POLYETHYLENE GLYCOL 400; SORBITOL; GLYCERIN

5820074 Publix Enamel Guard Intensive (8015074)

ACTIVE INGREDIENT

potassium nitrate 5%

Sodium fluoride 0.25% (0.15% w/v fluoride ion)

PURPOSE

Antihypersensitivity

Anticavity

INDICATIONS AND USAGE

builds increasing protection against painful sensitivity of the teeth to cold, heat, acids, sweets or contact * aids in the prevention of dental cavities

When using this product, of iffitation occurs discontine use.

Stop use and ask a dentist if the problem persists or worsen. Sensitive teeth may indicate a serious problem that many need prompt care by a dentist.* pain/sensitivty still persists after 4 weeks of use.

Keep out of reach of children. If more than used for brushing is accidently swallowed, get medical help or contact a Posion Control Center right away.

DOSAGE AND ADMINISTRATION

adults and children 12 years of age and older: apply at least a 1-inch strip of the product onto a soft bristle toothbrush * brush teeth thoroughly for at least one minute twice a day (morning and evening), and not more than 3 times a day, or as recommended by a dentist or doctor. Make sure to brush all sensitive areas of the teeth. Minimize swallowing. Spit out after brushing.*children under 12 years of age: Consult a dentist or doctor.

INACTIVE INGREDIENT

water, hydrated silica, sorbitol, glycerin, PEG-8, flavor, cocamidopropyl betaine, titanium dioxide, xanthan gum, sodium saccharin, sodium hydroxide